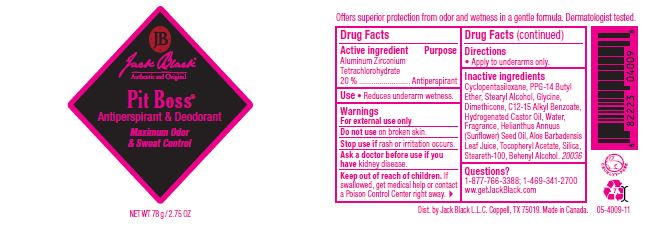 DRUG LABEL: Pit Boss Antiperspirant and Deodorant
NDC: 66738-706 | Form: STICK
Manufacturer: Jack Black L.L.C.
Category: otc | Type: HUMAN OTC DRUG LABEL
Date: 20260107

ACTIVE INGREDIENTS: ALUMINUM ZIRCONIUM TRICHLOROHYDRATE 20 g/100 g
INACTIVE INGREDIENTS: CYCLOMETHICONE 5; PPG-14 BUTYL ETHER; STEARYL ALCOHOL; ALKYL (C12-15) BENZOATE; DIMETHICONE; HYDROGENATED CASTOR OIL; BEHENYL ALCOHOL; STEARETH-100; SUNFLOWER OIL; .ALPHA.-TOCOPHEROL ACETATE; ALOE VERA LEAF; SILICON DIOXIDE

Jack Black Pit Boss Antiperspirant & Deodorant

Active Ingredient

Aluminum Zirconium Tretrachlorohydrate 20%

Purpose

Antiperspirant

Uses

Helps reduce underarm wetness. Provides long lasting odor protection.

Warnings

For external use only. Ask a doctor before use if you have kidney disease.

When using this product avoid contact with the eyes. Do not apply to broken skin.

Stop use and ask a doctor if rash or irritation develops or persists for more than seven days.

Keep out of the reach of children.

If swallowed, get medical help or contact a Poison Control Center immediately.

DOSAGE AND ADMINISTRATION

Apply to underarms only.

INACTIVE INGREDIENT

Other Ingredients: Cyclopentasiloxane, PPG-14 Butyl Ether, Stearyl Alcohol, C12-15 Alkyl Benzoate, Dimethicone, Hydrogenated Castor Oil, Fragrance, Behenyl Alcohol, Helianthus Annuus (Sunflower) Seed Oil, Glycerin, Steareth-100, Tocopheryl Acetate, Aloe Barbadensis Leaf Juice, Silica

QUESTIONS

Questions? 1-877-766-3388, 1-469-341-2700, www.getJackBlack.com